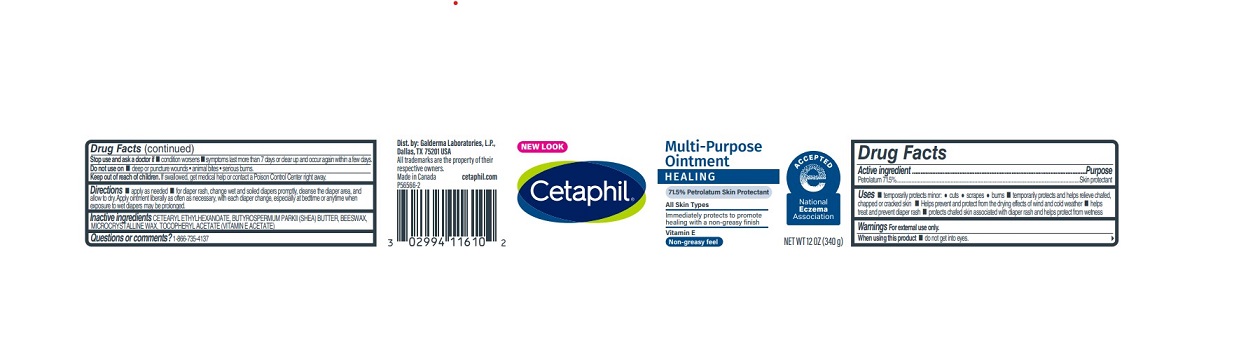 DRUG LABEL: Cetaphil Healing
NDC: 0299-4116 | Form: OINTMENT
Manufacturer: Galderma Laboratories, L.P.
Category: otc | Type: HUMAN OTC DRUG LABEL
Date: 20240313

ACTIVE INGREDIENTS: Petrolatum 715 mg/1 g
INACTIVE INGREDIENTS: Cetearyl Ethylhexanoate; Shea Butter; Yellow Wax; Microcrystalline Wax; .Alpha.-Tocopherol Acetate

Drug Facts

Active ingredient......Purpose

Petrolatum 71.5%......Skin Protectant

Uses

● temporarily protects minor:
● cuts ● scrapes ● burns
● temporary protects and helps relieve chafed, chapped or cracked skin
● helps prevent and protect from the drying effects of wind and cold weather
● helps treat and prevent diaper rash
● protects chafed skin associated with diaper rash and helps protect from wetness

Warnings

For external use only.

When using this product ● do not get into eyes.

Stop use and ask a doctor if ● condition worsens ● symptoms last more than 7 days or clear up and occur again within a few days.

Do not use on ● deep or puncture wounds ● animal bites ● serious burns

Keep out of reach of children. If swallowed, get medical help or contact a Poison Control Center right away.

Directions

● apply as needed
● for diaper rash, change wet and soiled diapers promptly, cleanse the diaper area, and allow to dry. Apply ointment liberally as often as necessary, with each diaper change, especially at bedtime or anytime when exposure to wet diapers may be prolonged.

Inactive Ingredients

CETEARYL ETHYLHEXANOATE, BUTYROSPERMUM PARKII (SHEA) BUTTER, BEESWAX, MICROCRYSTALLINE WAX, TOCOPHERYL ACETATE (VITAMIN E ACETATE)

Questions?

1-866-735-4137

Distributed By:
Galderma Laboratories, L.P.
Dallas, TX 75201 USA

All trademarks are the property of their respective owners.

Made in Canada

cetaphil.com

PRINCIPLE DISPLAY PANEL - 12 OZ (340g) jar

NEW LOOK
Cetaphil®

Multi-Purpose
Ointment
HEALING
71.5% Petrolatum Skin Protectant

All Skin Types

Immediately protects to promote
healing with a non-greasy finish

Vitamin E
Non-greasy feel

NATIONAL ECZEMA
ASSOCIATION LOGO
NET WT 12 OZ (340 g)
P56566-2